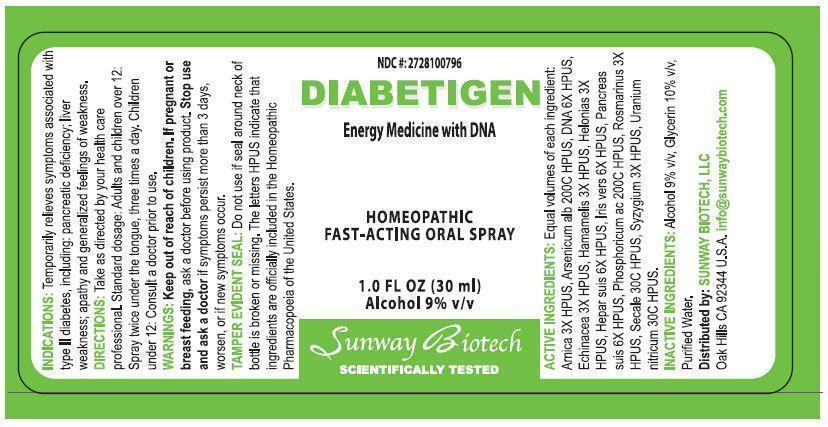 DRUG LABEL: Diabetigen
NDC: 27281-007 | Form: SPRAY
Manufacturer: Sunway Biotech LLC
Category: homeopathic | Type: HUMAN OTC DRUG LABEL
Date: 20131209

ACTIVE INGREDIENTS: ARNICA MONTANA 1.5 [hp_C]/30 mL; ARSENIC TRIOXIDE 200 [hp_C]/30 mL; HERRING SPERM DNA 3 [hp_C]/30 mL; ECHINACEA, UNSPECIFIED 1.5 [hp_C]/30 mL; HAMAMELIS VIRGINIANA LEAF 1.5 [hp_C]/30 mL; CHAMAELIRIUM LUTEUM ROOT 1.5 [hp_C]/30 mL; PORK LIVER 3 [hp_C]/30 mL; IRIS VERSICOLOR ROOT 3 [hp_C]/30 mL; SUS SCROFA PANCREAS 3 [hp_C]/30 mL; PHOSPHORIC ACID 200 [hp_C]/30 mL; ROSMARINUS OFFICINALIS FLOWERING TOP 1.5 [hp_C]/30 mL; CLAVICEPS PURPUREA SCLEROTIUM 30 [hp_C]/30 mL; SYZYGIUM CUMINI SEED 1.5 [hp_C]/30 mL; URANYL NITRATE HEXAHYDRATE 30 [hp_C]/30 mL
INACTIVE INGREDIENTS: ALCOHOL; GLYCERIN; WATER

ACTIVE INGREDIENT

Active Ingredients: Equal volumes of each ingredient: Arnica 3X HPUS, Arsenicum Alb 200C HPUS, DNA 6X HPUS, Echinacea 3X HPUS, Hamamelis 3X HPUS, Helonias 3X HPUS, Hepar Suis 6X HPUS, Iris Vers 6X HPUS, Pancreas Suis 6X HPUS, Phosphoricum Ac 200C HPUS, Rosmarinus 3X HPUS, Secale 30C HPUS, Syzygium 3X HPUS, Uranium Nitricum 30C HPUS.

Keep out of reach of children.

PURPOSE

NDC #: 2728100796

DIABETIGEN

Energy Medicine with DNA

Homeopathic Fast-Acting Oral Spray

1.0 Fl. Oz. (30 mL)

Alcohol 9% v/v

INDICATIONS AND USAGE

Indications: Temporarily relieves symptoms associated with type II diabetes, including: pancreatic deficiency; liver weakness; apathy and generalized feelings of weakness.

DOSAGE AND ADMINISTRATION

Directions: Take as directed by your health care professional. Standard dosage: Adults and children over 12: Spray twice under the tongue, three times a day. Children under 12: Consult a doctor prior to use.

WARNINGS

Warnings: Keep out of reach of children. If pregnant or breast feeding, ask a doctor before using product. Stop use and ask a doctor if symptoms persis more than 3 days, worsen, or if new symptoms occur.

OTHER SAFETY INFORMATION

Tamper Evident Seal: Do not use if seal around neck of bottle is broken or missing. The letters HPUS indicate that ingredients are officially included in the Homeopathic Pharmacopoeia of the United States.

Distributed by:

SUNWAY BIOTECH LLC

Oak HIlls, CA 92344 U.S.A.

info@sunwaybiotech.com

INACTIVE INGREDIENT

Inactive Ingredients: Alcohol 9% v/v, Glycerin 10% v/v, Purified Water.